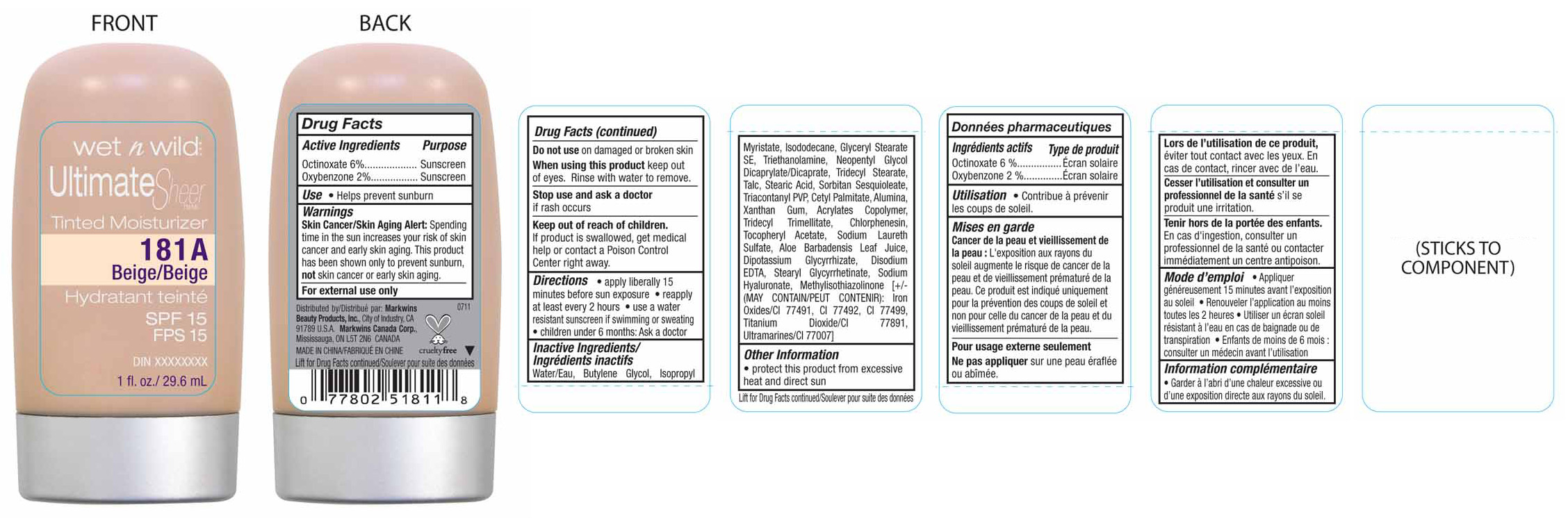 DRUG LABEL: wet n wild
NDC: 12027-104 | Form: LIQUID
Manufacturer: Markwins Beauty Products, Inc 
Category: otc | Type: HUMAN OTC DRUG LABEL
Date: 20111119

ACTIVE INGREDIENTS: OCTINOXATE 6 mL/100 mL; OXYBENZONE 2 mL/100 mL
INACTIVE INGREDIENTS: WATER; BUTYLENE GLYCOL; ISOPROPYL MYRISTATE; ISODODECANE; GLYCERYL MONOSTEARATE; TROLAMINE; TRIDECYL STEARATE; TALC; STEARIC ACID; SORBITAN SESQUIOLEATE; TRIACONTANYL PVP (WP-660); CETYL PALMITATE; ALUMINUM OXIDE; XANTHAN GUM; TRIDECYL TRIMELLITATE; CHLORPHENESIN ; ALPHA-TOCOPHEROL ACETATE; SODIUM LAURETH SULFATE; ALOE VERA LEAF; GLYCYRRHIZINATE DIPOTASSIUM; EDETATE DISODIUM; STEARYL GLYCYRRHETINATE; HYALURONATE SODIUM; METHYLISOTHIAZOLINONE; FERRIC OXIDE RED; TITANIUM DIOXIDE

Active Ingredients
Octinoxate 6%
Oxybenzone 2%

INDICATIONS AND USAGE

Use• Helps prevent sunburn

Warnings
Skin Cancer/Skin Aging Alert: Spending time in the sun increases your risk of skin cancer and early skin aging. This product has been shown only to help prevent sunburn, not skin cancer or skin aging.
For external use only.
Do not use on damaged or broken skin
When using this product keep out of eyes. Rinse with water to remove.

Stop use and ask a doctor
if rash occurs

Keep out of reach of children.
If product is swallowed, get medical help or contact a Poison Control Center right away.

INDICATIONS AND USAGE

Directions • apply liberally 15 minutes before sun exposure • reapply at least every 2 hours
• use a water resistant sunscreen if swimming or sweating
• children under 6 months: Ask a doctor

INACTIVE INGREDIENT

Inactive Ingredients/Ingredients inactifs Water/Eau, Butylene Glycol, Isopropyl Myristate, Isododecane, Glyceryl Stearate SE, Triethanolamine, Neopentyl Glycol Dicaprylate/Dicaprate, Tridecyl Stearate, Talc, Stearic Acid, Sorbitan Sesquioleate, Triacontanyl PVP, Cetyl Palmitate, Alumina, Xanthan Gum, Acrylates Copolymer, Tridecyl Trimellitate, Chlorphenesin, Tocopheryl Acetate, Sodium Laureth Sulfate, Aloe Barbadensis Leaf Juice, Dipotassium Glycyrrhizate, Disodium EDTA, Stearyl Glycyrrhetinate, Sodium Hyaluronate, Methylisothiazolinone
(MAY CONTAIN/PEUT CONTENIR): Iron Oxides/CI 77491, CI 77492, CI 77499, Titanium Dioxide/CI 77891, Ultramarines/CI 77007 77891, Yellow 6 Lake/CI 15985, Yellow 10 Lake/CI 47005, Zinc Oxide/CI 77947)

Package Label